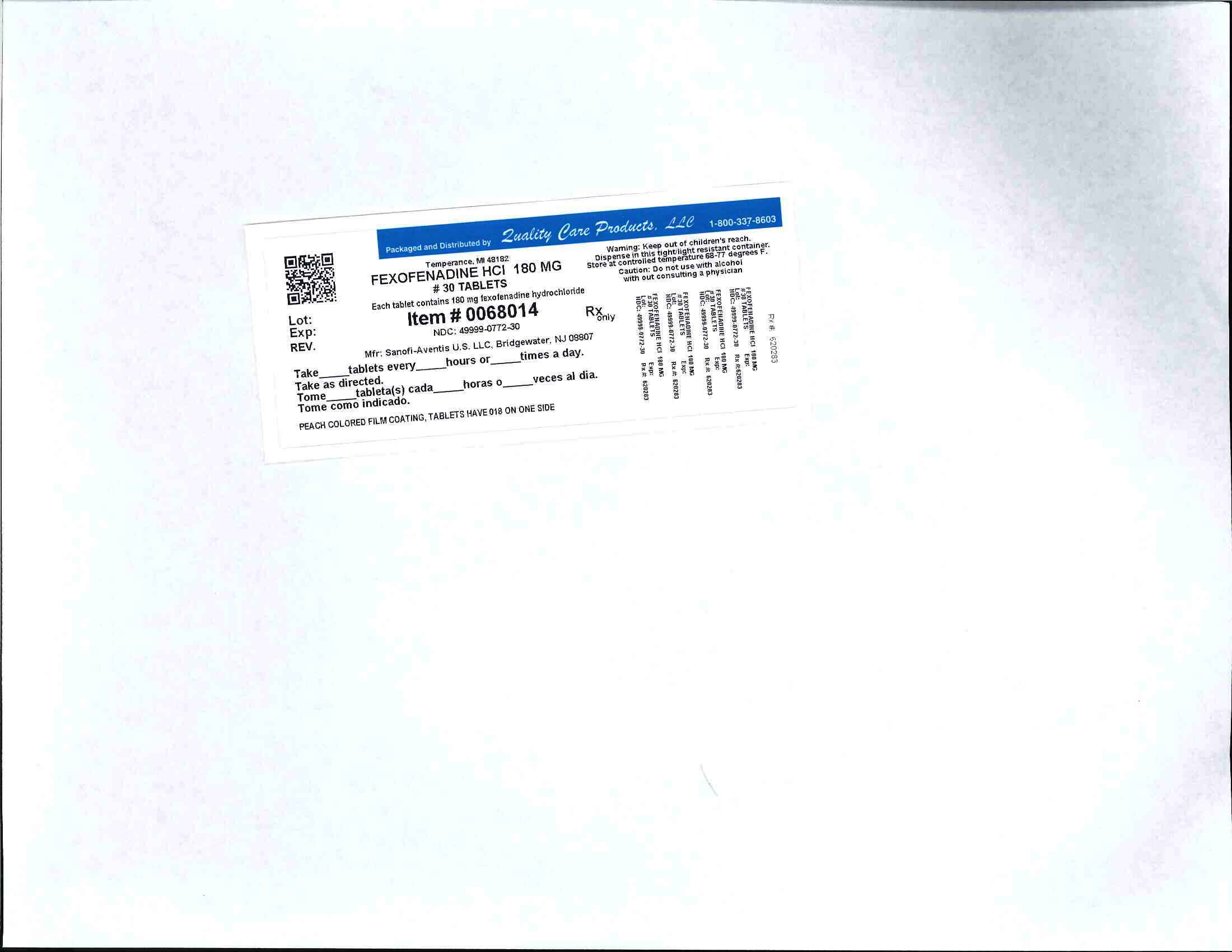 DRUG LABEL: Fexofenadine Hydrochloride
NDC: 49999-772 | Form: TABLET, FILM COATED
Manufacturer: Lake Erie Medical DBA Quality Care Products LLC
Category: prescription | Type: HUMAN PRESCRIPTION DRUG LABEL
Date: 20100607

ACTIVE INGREDIENTS: FEXOFENADINE HYDROCHLORIDE 180 mg/1 1
INACTIVE INGREDIENTS: CROSCARMELLOSE SODIUM; MAGNESIUM STEARATE; CELLULOSE, MICROCRYSTALLINE; STARCH, CORN

Fexofenadine HCL 180 mg

DESCRIPTION
Fexofenadine hydrochloride is a histamine H1-receptor antagonist with the chemical name (±)-4-[1 hydroxy-4-[4-(hydroxydiphenylmethyl)-1-piperidinyl]-butyl]-α,α-dimethyl benzeneacetic acid hydrochloride. It has the following chemical structure
The molecular weight is 538.13 and the empirical formula is C32H39NO4•HCl.
Fexofenadine hydrochloride is a white to off-white crystalline powder. It is freely soluble in methanol and ethanol, slightly soluble in chloroform and water, and insoluble in hexane. Fexofenadine hydrochloride is a racemate and exists as a zwitterion in aqueous media at physiological pH.
Fexofenadine hydrochloride is formulated as a tablet for oral administration. Each tablet contains 30, 60, or 180 mg fexofenadine hydrochloride (depending on the dosage strength) and the following excipients: croscarmellose sodium, magnesium stearate, microcrystalline cellulose, and pregelatinized starch. The aqueous tablet film coating is made from hypromellose, iron oxide blends, polyethylene glycol, povidone, silicone dioxide, and titanium dioxide.

CLINICAL PHARMACOLOGYMechanism of Action

Fexofenadine hydrochloride, the major active metabolite of terfenadine, is an antihistamine with selective peripheral H1-receptor antagonist activity. Both enantiomers of fexofenadine hydrochloride displayed approximately equipotent antihistaminic effects. Fexofenadine hydrochloride inhibited antigen-induced bronchospasm in sensitized guinea pigs and histamine release from peritoneal mast cells in rats. The clinical significance of these findings is unknown. In laboratory animals, no anticholinergic or alpha1-adrenergic blocking effects were observed. Moreover, no sedative or other central nervous system effects were observed. Radiolabeled tissue distribution studies in rats indicated that fexofenadine does not cross the blood-brain barrier.

INDICATIONS AND USAGESeasonal Allergic Rhinitis

Fexofenadine Hydrochloride Tablets are indicated for the relief of symptoms associated with seasonal allergic rhinitis in adults and children 6 years of age and older. Symptoms treated effectively were sneezing, rhinorrhea, itchy nose/palate/throat, itchy/watery/red eyes.

Chronic Idiopathic Urticaria

Fexofenadine Hydrochloride Tablets are indicated for treatment of uncomplicated skin manifestations of chronic idiopathic urticaria in adults and children 6 years of age and older. It significantly reduces pruritus and the number of wheals.

CONTRAINDICATIONS

Fexofenadine Hydrochloride Tablets are contraindicated in patients with known hypersensitivity to any of its ingredients.

PRECAUTIONS
Information for Patients
Patients taking Fexofenadine Hydrochloride Tablets should receive the following information:

Fexofenadine Hydrochloride Tablets are prescribed for the relief of symptoms of seasonal allergic rhinitis or for the relief of symptoms of chronic idiopathic urticaria (hives). Patients should be instructed to take Fexofenadine Hydrochloride Tablets only as prescribed. Do not exceed the recommended dose. If any untoward effects occur while taking Fexofenadine Hydrochloride Tablets, discontinue use and consult the doctor.

The product should not be used by patients who are hypersensitive to it or to any of its ingredients.

Patients should be told that this product should be used in pregnancy or lactation only if the potential benefit justifies the potential risk to the fetus or nursing infant.

Patients should be advised to take the tablet with water. Patients should also be advised to store the medication in a tightly closed container in a cool, dry place, away from children.

Drug Interaction with Erythromycin and Ketoconazole
Fexofenadine has been shown to exhibit minimal (ca. 5%) metabolism. However, co-administration of fexofenadine hydrochloride with either ketoconazole or erythromycin led to increased plasma concentrations of fexofenadine. Fexofenadine had no effect on the pharmacokinetics of either erythromycin or ketoconazole. In 2 separate studies, fexofenadine hydrochloride 120 mg twice daily (240 mg total daily dose) was co-administered with either erythromycin 500 mg every 8 hours or ketoconazole 400 mg once daily under steady-state conditions to healthy volunteers (n=24, each study). No differences in adverse events or QTc interval were observed when subjects were administered fexofenadine hydrochloride alone or in combination with either erythromycin or ketoconazole. The findings of these studies are summarized in the following table:

Effects on steady-state fexofenadine pharmacokinetics after 7 days of co-administration with fexofenadine hydrochloride 120 mg every 12 hours (two times the recommended twice daily dose) in healthy volunteers (n=24)
Concomitant Drug | CmaxSS (Peak plasma concentration) | AUCss(0–12h) (Extent of systemic exposure)
Erythromycin | +82% | +109%
(500 mg every 8 hrs)
Ketoconazole | +135% | +164%
(400 mg once daily)

The changes in plasma levels were within the range of plasma levels achieved in adequate and well-controlled clinical trials.

The mechanism of these interactions has been evaluated in in vitro, in situ, and in vivo animal models. These studies indicate that ketoconazole or erythromycin co-administration enhances fexofenadine gastrointestinal absorption. This observed increase in the bioavailability of fexofenadine may be due to transport-related effects, such as p-glycoprotein. In vivo animal studies also suggest that in addition to enhancing absorption, ketoconazole decreases fexofenadine gastrointestinal secretion, while erythromycin may also decrease biliary excretion.

Drug Interactions with Antacids
Administration of 120 mg of fexofenadine hydrochloride (2 × 60 mg capsule) within 15 minutes of an aluminum and magnesium containing antacid (Maalox®) decreased fexofenadine AUC by 41% and Cmax by 43%. Fexofenadine hydrochloride should not be taken closely in time with aluminum and magnesium containing antacids.
Interactions with Fruit Juices
Fruit juices such as grapefruit, orange and apple may reduce the bioavailability and exposure of fexofenadine. This is based on the results from 3 clinical studies using histamine induced skin wheals and flares coupled with population pharmacokinetic analysis. The size of wheal and flare were significantly larger when fexofenadine hydrochloride was administered with either grapefruit or orange juices compared to water. Based on the literature reports, the same effects may be extrapolated to other fruit juices such as apple juice. The clinical significance of these observations is unknown. In addition, based on the population pharmacokinetics analysis of the combined data from grapefruit and orange juices studies with the data from a bioequivalence study, the bioavailability of fexofenadine was reduced by 36%. Therefore, to maximize the effects of fexofenadine, it is recommended that Fexofenadine hydrochloride should be taken with water (see Dosage and Administration).
CARCINOGENESIS, MUTAGENESIS, IMPAIRMENT OF FERTILITY

The carcinogenic potential and reproductive toxicity of fexofenadine hydrochloride were assessed using terfenadine studies with adequate fexofenadine hydrochloride exposure (based on plasma area-under-the-concentration vs. time [AUC] values). No evidence of carcinogenicity was observed in an 18-month study in mice and in a 24-month study in rats at oral doses up to 150 mg/kg of terfenadine (which led to fexofenadine exposures that were approximately 3 and 5 times the exposure from the maximum recommended human daily oral dose of fexofenadine hydrochloride in adults [180 mg] and children [60 mg] respectively .

In in vitro (Bacterial Reverse Mutation, CHO/HGPRT Forward Mutation, and Rat Lymphocyte Chromosomal Aberration assays) and in vivo (Mouse Bone Marrow Micronucleus assay) tests, fexofenadine hydrochloride revealed no evidence of mutagenicity.

In rat dietary fertility studies, dose-related reductions in implants and increases in postimplantation losses were observed at an oral dose of 150 mg/kg of terfenadine (which led to fexofenadine hydrochloride exposures that were approximately 3 times the exposure of the maximum recommended human daily oral dose of 180 mg fexofenadine hydrochloride). In mice, fexofenadine hydrochloride produced no effect on male or female fertility at average dietary doses up to 4438 mg/kg (approximately 10 times the maximum recommended human daily oral dose of fexofenadine hydrochloride 180 mg based on comparison of AUCs).

PREGNANCY

Teratogenic Effects

Category C.

There was no evidence of teratogenicity in rats or rabbits at oral doses of terfenadine up to 300 mg/kg (which led to fexofenadine exposures that were approximately 3 and 30 times, respectively, the exposure from the maximum recommended human daily oral dose of fexofenadine hydrochloride of 180 mg based on comparison of AUCs).

In mice, no adverse effects and no teratogenic effects during gestation were observed with fexofenadine at dietary doses up to 3730 mg/kg (approximately 15 times the maximum recommended human daily oral dose of fexofenadine hydrochloride 180 mg based on comparison of AUCs).

There are no adequate and well controlled studies in pregnant women. Fexofenadine should be used during pregnancy only if the potential benefit justifies the potential risk to the fetus.

Nonteratogenic Effects

Dose-related decreases in pup weight gain and survival were observed in rats exposed to an oral dose of 150 mg/kg of terfenadine (approximately 3 times the maximum recommended human daily oral dose of fexofenadine hydrochloride of 180 mg in adults based on comparison of fexofenadine hydrochloride AUCs).

NURSING MOTHERS
It is not known if fexofenadine is excreted in human milk. There are no adequate and well-controlled studies in women during lactation. Because many drugs are excreted in human milk, caution should be exercised when fexofenadine hydrochloride is administered to a nursing woman.
PEDIATRIC USE

The recommended dose in patients 6 to 11 years of age is based on cross-study comparison of the pharmacokinetics of fexofenadine hydrochloride in adults and pediatric subjects and on the safety profile of fexofenadine hydrochloride in both adult and pediatric subjects at doses equal to or higher than the recommended doses.

The safety of fexofenadine hydrochloride tablets at a dose of 30 mg twice daily has been demonstrated in 438 pediatric subjects 6 to 11 years of age in two placebo-controlled 2-week seasonal allergic rhinitis trials. The safety of fexofenadine hydrochloride for the treatment of chronic idiopathic urticaria in subjects 6 to 11 years of age is based on cross-study comparison of the pharmacokinetics of fexofenadine hydrochloride in adult and pediatric subjects and on the safety profile of fexofenadine in both adult and pediatric subjects at doses equal to or higher than the recommended dose.

The effectiveness of fexofenadine hydrochloride for the treatment of seasonal allergic rhinitis in subjects 6 to 11 years of age was demonstrated in 1 trial (n=411) in which fexofenadine hydrochloride tablets 30 mg twice daily significantly reduced total symptom scores compared to placebo, along with extrapolation of demonstrated efficacy in subjects aged 12 years and above, and the pharmacokinetic comparisons in adults and children. The effectiveness of fexofenadine hydrochloride for the treatment of chronic idiopathic urticaria in patients 6 to 11 years of age is based on an extrapolation of the demonstrated efficacy of fexofenadine hydrochloride in adults with this condition and the likelihood that the disease course, pathophysiology and the drug's effect are substantially similar in children to that of adult patients.

Three clinical safety studies comparing 15 mg twice daily (n=85) and 30 mg twice daily (n=330) of an experimental formulation of fexofenadine to placebo (n=430) have been conducted in pediatric subjects aged 6 months to 5 years. In general, fexofenadine hydrochloride was well tolerated in these studies. No unexpected adverse events were seen given the known safety profile of fexofenadine and likely adverse reactions for this patient population. (See ADVERSE REACTIONS and CLINICAL PHARMACOLOGY.)

The safety and effectiveness of fexofenadine hydrochloride in pediatric patients under 6 years of age have not been established.

GERIATRIC USE
Clinical studies of fexofenadine hydrochloride tablets and capsules did not include sufficient numbers of subjects aged 65 years and over to determine whether this population responds differently from younger subjects. Other reported clinical experience has not identified differences in responses between the geriatric and younger subjects. This drug is known to be substantially excreted by the kidney, and the risk of toxic reactions to this drug may be greater in patients with impaired renal function. Because elderly patients are more likely to have decreased renal function, care should be taken in dose selection, and it may be useful to monitor renal function. (See CLINICAL PHARMACOLOGY).

ADVERSE REACTIONS
Seasonal Allergic Rhinitis
Adults

In placebo-controlled seasonal allergic rhinitis clinical trials in subjects 12 years of age and older, which included 2461 subjects receiving fexofenadine hydrochloride capsules at doses of 20 mg to 240 mg twice daily, adverse events were similar in fexofenadine hydrochloride- and placebo-treated subjects. All adverse events that were reported by greater than 1% of subjects who received the recommended daily dose of fexofenadine hydrochloride (60 mg capsules twice daily), and that were more common with fexofenadine hydrochloride than placebo, are listed in Table 1.

In a placebo-controlled clinical study in the United States, which included 570 subjects aged 12 years and older receiving fexofenadine hydrochloride tablets at doses of 120 or 180 mg once daily, adverse events were similar in fexofenadine hydrochloride- and placebo-treated subjects. Table 1 also lists adverse experiences that were reported by greater than 2% of subjects treated with fexofenadine hydrochloride tablets at doses of 180 mg once daily and that were more common with fexofenadine hydrochloride than placebo.

The incidence of adverse events, including drowsiness, was not dose-related and was similar across subgroups defined by age, gender, and race.

Table 1 Adverse experiences in subjects aged 12 years and older reported in placebo-controlled seasonal allergic rhinitis clinical trials in the United States
Twice- daily dosing with fexofenadine capsules
at rates of greater than 1%
Adverse experience | Fexofenadine 60 mg Twice Daily (n=679) | Placebo Twice Daily (n=671)
Viral Infection (cold, flu) | 2.5% | 1.5%
Nausea | 1.6% | 1.5%
Dysmenorrhea | 1.5% | 0.3%
Drowsiness | 1.3% | 0.9%
Dyspepsia | 1.3% | 0.6%
Fatigue | 1.3% | 0.9%
Once daily dosing with fexofenadine hydrochloride tablets
at rates of greater than 2%
Adverse experience | Fexofenadine 180 mg Once Daily (n=283) | Placebo (n=293)
Headache | 10.6% | 7.5%
Upper Respiratory Tract Infection | 3.2% | 3.1%
Back Pain | 2.8% | 1.4%

The frequency and magnitude of laboratory abnormalities were similar in fexofenadine hydrochloride- and placebo-treated subjects.

Pediatrics

Table 2 lists adverse experiences in subjects aged 6 to 11 years of age which were reported by greater than 2% of subjects treated with fexofenadine hydrochloride tablets at a dose of 30 mg twice daily in placebo-controlled seasonal allergic rhinitis studies in the United States and Canada that were more common with fexofenadine hydrochloride than placebo.

Table 2 Adverse experiences reported in placebo-controlled seasonal allergic rhinitis studies in pediatric subjects aged 6 to 11 in the United States and Canada at rates of greater than 2%
Adverse experience | Fexofenadine 30 mg Twice Daily (n=209) | Placebo (n=229)
Headache | 7.2% | 6.6%
Accidental Injury | 2.9% | 1.3%
Coughing | 3.8% | 1.3%
Fever | 2.4% | 0.9%
Pain | 2.4% | 0.4%
Otitis Media | 2.4% | 0.0%
Upper Respiratory Tract Infection | 4.3% | 1.7%

Three clinical safety studies in 845 children aged 6 months to 5 years comparing 15 mg twice daily (n=85) and 30 mg twice daily (n=330) of an experimental formulation of fexofenadine to placebo (n=430) have been conducted. In general, fexofenadine hydrochloride was well tolerated in these studies. No unexpected adverse events were seen given the known safety profile of fexofenadine and likely adverse reactions for this patient population. (See PRECAUTIONS Pediatric Use.)
Chronic Idiopathic Urticaria
Adverse events reported by subjects 12 years of age and older in placebo-controlled chronic idiopathic urticaria studies were similar to those reported in placebo-controlled seasonal allergic rhinitis studies. In placebo-controlled chronic idiopathic urticaria clinical trials, which included 726 subjects 12 years of age and older receiving fexofenadine hydrochloride tablets at doses of 20 to 240 mg twice daily, adverse events were similar in fexofenadine hydrochloride- and placebo-treated patients. Table 3 lists adverse experiences in subjects aged 12 years and older which were reported by greater than 2% of subjects treated with fexofenadine hydrochloride 60 mg tablets twice daily in controlled clinical studies in the United States and Canada and that were more common with fexofenadine hydrochloride than placebo.
In a placebo-controlled clinical study in the United States, which included 167 subjects aged 12 years and older receiving fexofenadine hydrochloride 180 mg tablets, adverse events were similar in fexofenadine hydrochloride- and placebo-treated subjects. Table 3 also lists adverse experiences that were reported by greater than 2% of subjects treated with fexofenadine hydrochloride tablets at doses of 180 mg once daily and that were more common with fexofenadine hydrochloride than placebo.

The safety of fexofenadine hydrochloride in the treatment of chronic idiopathic urticaria in pediatric patients 6 to 11 years of age is based on the safety profile of fexofenadine hydrochloride in adults and adolescent patients at doses equal to or higher than the recommended dose (see Pediatric Use).

Table 3 Adverse experiences reported in subjects 12 years of age and older in placebo-controlled chronic idiopathic urticaria studies
Twice-daily dosing with fexofenadine hydrochloride in studies
in the United States and Canada at rates of greater than 2%
Adverse experience | Fexofenadine 60 mg Twice Daily (n=191) | Placebo (n=183)
Dyspepsia | 4.7% | 4.4%
Myalgia | 2.6% | 2.2%
Back Pain | 2.1% | 1.1%
Dizziness | 2.1% | 1.1%
Pain in extremity | 2.1% | 0.0%
Once-daily dosing with fexofenadine hydrochloride in a study
in the United States at rates of greater than 2%
Adverse experience | Fexofenadine 180 mg Once Daily (n=167) | Placebo (n=92)
Headache | 4.8% | 3.3%
Nasopharyngitis | 2.4% | 2.2%
Upper respiratory tract infection | 2.4% | 2.2%

Events that have been reported during controlled clinical trials involving seasonal allergic rhinitis and chronic idiopathic urticaria subjects with incidences less than 1% and similar to placebo and have been rarely reported during postmarketing surveillance include: insomnia, nervousness, and sleep disorders or paroniria. In rare cases, rash, urticaria, pruritus and hypersensitivity reactions with manifestations such as angioedema, chest tightness, dyspnea, flushing and systemic anaphylaxis have been reported.

OVERDOSAGE

Reports of fexofenadine hydrochloride overdose have been infrequent and contain limited information. However, dizziness, drowsiness, and dry mouth have been reported. Single doses of fexofenadine hydrochloride up to 800 mg (6 healthy volunteers at this dose level), and doses up to 690 mg twice daily for 1 month (3 healthy volunteers at this dose level) or 240 mg once daily for 1 year (234 healthy volunteers at this dose level) were administered without the development of clinically significant adverse events as compared to placebo.

In the event of overdose, consider standard measures to remove any unabsorbed drug. Symptomatic and supportive treatment is recommended. Following administration of terfenadine, hemodialysis did not effectively remove fexofenadine, the major active metabolite of terfenadine, from blood (up to 1.7% removed).

No deaths occurred at oral doses of fexofenadine hydrochloride up to 5000 mg/kg in mice (110 times the maximum recommended human daily oral dose in adults and 200 times the maximum recommended human daily oral dose in children based on mg/m^2) and up to 5000 mg/kg in rats (230 times the maximum recommended human daily oral dose in adults and 400 times the maximum recommended human daily oral dose in children based on mg/m^2). Additionally, no clinical signs of toxicity or gross pathological findings were observed. In dogs, no evidence of toxicity was observed at oral doses up to 2000 mg/kg (300 times the maximum recommended human daily oral dose in adults and 530 times the maximum recommended human daily oral dose in children based on mg/m^2).

DOSAGE AND ADMINISTRATION
Seasonal Allergic Rhinitis
Adults and Children 12 Years and Older

The recommended dose of Fexofenadine Hydrochloride Tablets is 60 mg twice daily, or 180 mg once daily with water. A dose of 60 mg once daily is recommended as the starting dose in patients with decreased renal function (see CLINICAL PHARMACOLOGY).

Children 6 to 11 Years

The recommended dose of Fexofenadine Hydrochloride Tablets is 30 mg twice daily with water. A dose of 30 mg once daily is recommended as the starting dose in pediatric patients with decreased renal function (see CLINICAL PHARMACOLOGY).

Chronic Idiopathic Urticaria
Adults and Children 12 Years and Older

The recommended dose of Fexofenadine Hydrochloride Tablets is 60 mg twice daily or 180 mg once daily with water. A dose of 60 mg once daily is recommended as the starting dose in patients with decreased renal function (see CLINICAL PHARMACOLOGY).

Children 6 to 11 Years

The recommended dose of Fexofenadine Hydrochloride Tablets is 30 mg twice daily with water. A dose of 30 mg once daily is recommended as the starting dose in pediatric patients with decreased renal function (see CLINICAL PHARMACOLOGY).

HOW SUPPLIED
Fexofenadine Hydrochloride Tablets 30 mg are available in HDPE bottles of 100 (NDC 66993-106-02) with a polypropylene screw cap containing a pulp/wax liner with heat-sealed foil inner seal.

Fexofenadine Hydrochloride Tablets 60 mg are available in HDPE bottles of 100 (NDC 66993-107-02) with a polypropylene screw cap containing a pulp/wax liner with heat-sealed foil inner seal and HDPE bottles of 500 (NDC 66993-104-04) with a polypropylene screw cap containing a pulp/wax liner with heat-sealed foil inner seal.

Fexofenadine Hydrochloride Tablets 180 mg are available in HDPE bottles of 100 (NDC 66993-109-02) with a polypropylene screw cap containing a pulp/wax liner with heat-sealed foil inner seal and HDPE bottles of 500 (NDC 66993-109-04) with a polypropylene screw cap containing a pulp/wax liner with heat-sealed foil inner seal.

Fexofenadine Hydrochloride Tablets are coated with a peach colored film coating. Tablets have the following unique identifiers: 30 mg tablets have 03 on one side, 60 mg tablets have 06 on one side, and 180 mg tablets have 018 on one side.

Store Fexofenadine Hydrochloride Tablets at controlled room temperature 20–25°C (68–77°F). (See USP Controlled Room Temperature). Fexofenadine Hydrochloride Tablets should be protected from excessive moisture.

Rev. August 2006
Manufactured by:
sanofi-aventis U.S. LLC.
Bridgewater, NJ 08807 USA

Manufactured for:
Prasco Laboratories
Cincinnati, OH 45249 USA

©2006 sanofi-aventis U.S. LLC.

Image of label